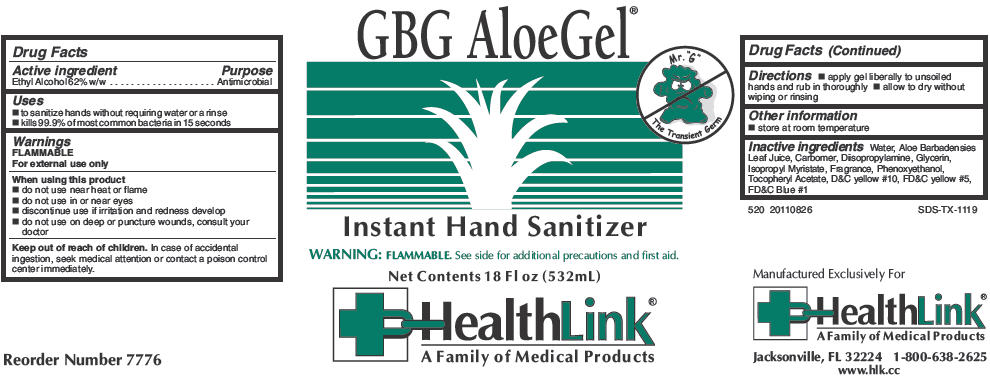 DRUG LABEL: GBG AloeGel Instant Hand Sanitizer
NDC: 63843-520 | Form: SOAP
Manufacturer: HealthLink
Category: otc | Type: HUMAN OTC DRUG LABEL
Date: 20180131

ACTIVE INGREDIENTS: ALCOHOL 0.62 mL/1 mL
INACTIVE INGREDIENTS: WATER; CARBOMER HOMOPOLYMER TYPE C (ALLYL PENTAERYTHRITOL CROSSLINKED); GLYCERIN; ALOE VERA LEAF; ISOPROPYL MYRISTATE; PHENOXYETHANOL; .ALPHA.-TOCOPHEROL ACETATE; DIISOPROPYLAMINE

GBG AloeGel® Instant Hand Sanitizer

Drug Facts

Active ingredient

Ethyl Alcohol 62% w/w

Purpose

Antimicrobial

Uses

- to sanitize hands without requiring water or a rinse
- kills 99.9% of most common bacteria in 15 seconds

Warnings

FLAMMABLE

For external use only

When using this product

- do not use near heat or flame
- do not use in or near eyes
- discontinue use if irritation and redness develop
- do not use on deep or puncture wounds, consult your doctor

Keep out of reach of children. In case of accidental ingestion, seek medical attention or contact a poison control center immediately.

Directions

- apply gel liberally to unsoiled hands and rub in thoroughly
- allow to dry without wiping or rinsing

Other information

- store at room temperature

Inactive ingredients

Water, Aloe Barbadensies Leaf Juice, Carbomer, Diisopropylamine, Glycerin, Isopropyl Myristate, Fragrance, Phenoxyethanol, Tocopheryl Acetate, D&C yellow #10, FD&C yellow #5, FD&C Blue #1

Manufactured Exclusively For
HealthLink®
A Family of Medical Products
Jacksonville, FL 32224

PRINCIPAL DISPLAY PANEL - 532 mL Bottle Label

GBG AloeGel®

Mr. "G"
The Transient Germ

Instant Hand Sanitizer

WARNING: FLAMMABLE. See side for additional precautions and first aid.

Net Contents 18 Fl oz (532mL)

HealthLink®
A Family of Medical Products